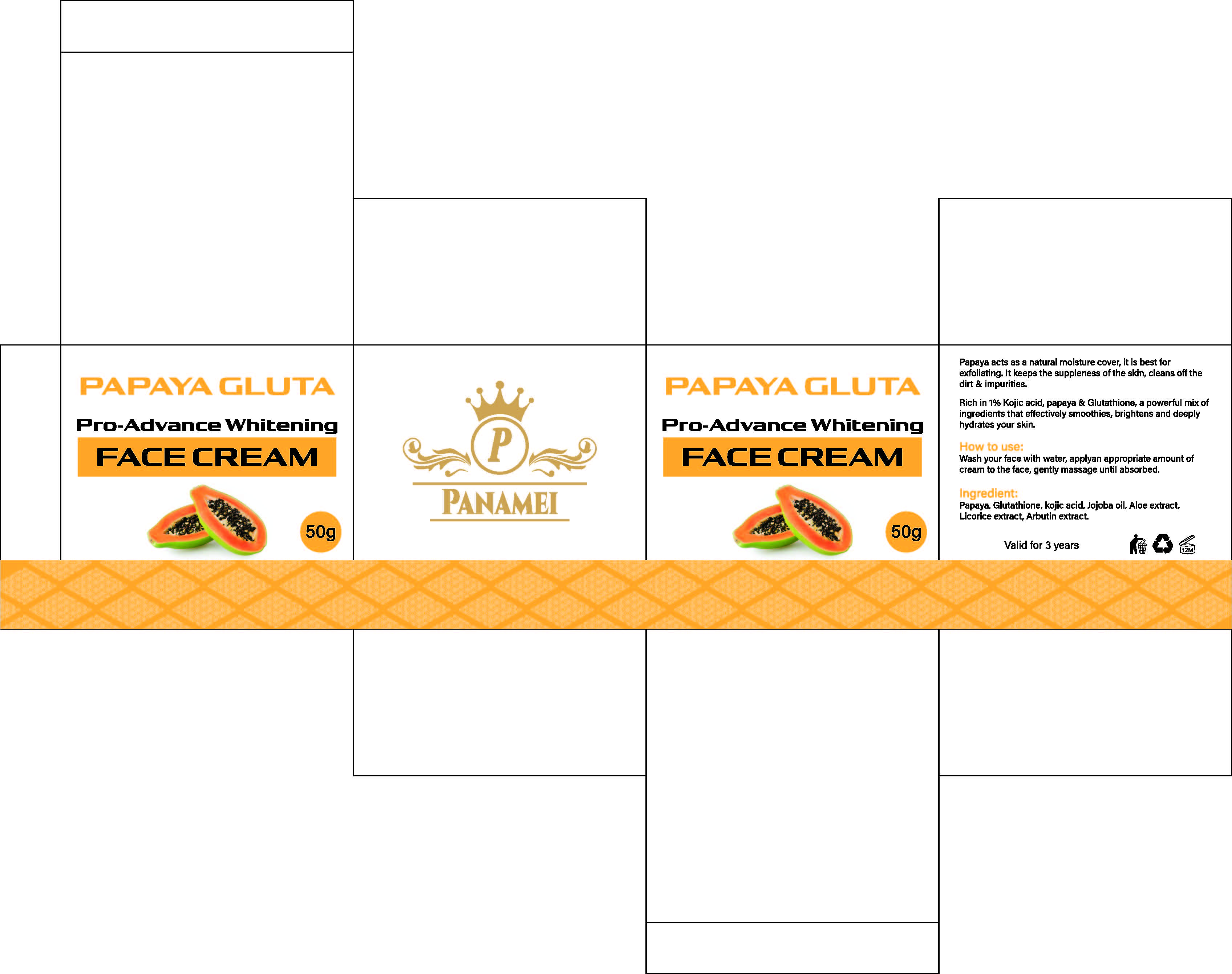 DRUG LABEL: PAPAYA GLUTA  FACECREAM
NDC: 84423-081 | Form: CREAM, AUGMENTED
Manufacturer: Guangzhou Kadiya Biotechnology Co., Ltd.
Category: otc | Type: HUMAN OTC DRUG LABEL
Date: 20250602

ACTIVE INGREDIENTS: CARICA PAPAYA (PAPAYA) FRUIT 1 g/50 g; CARICA PAPAYA (PAPAYA) SEED OIL 1.5 g/50 g
INACTIVE INGREDIENTS: MYRISTYL ALCOHOL; ALPHA-ARBUTIN; PEG-60 SORBITAN STEARATE; PALMITIC ACID; DIMETHICONE; STEAROLIC ACID; TRIETHANOLAMINE; PEG-75 LANOLIN; MINERAL OIL; CETYL ALCOHOL; DIETHYLENE GLYCOL MONOETHYL ETHER; DINICOTINAMIDE; TITANIUM DIOXIDE; MYRISTIC ACID; SODIUM CHLORIDE; WATER; PHENOXYETHANOL; ALLANTOIN; GLYCERYL STEARATE; GLYCERIN; LAURIC ACID; ALUMINA; CI 19140; PROPYLPARABEN; CI 15985; METHYLPARABEN

PURPOSE

For Facial Skin Moisturizing, Antioxidant, Blemish Removal, Whitening, Brightening

INACTIVE INGREDIENT

water
Glycerol
Mineral oil
Polydimethylsiloxane
Polysorbate -60
Palmitic acid
Ethoxy diethylene glycol
Lauric acid/myristic acid/palmitic acid/stearic acid glycerides
Stearol
Glycerol stearate
Nicotinamide
Titanium dioxide
Cetazol
Triethanolamine
PEG-75 lanolin
Allantoin
Methyl hydroxybenzoate
α -arbutin
Myristic acid
Propylparaben
(Daily-use) essence
Lauric acid
Alumina
Nutmeg alcohol
CI 19140
Sodium chloride
CI 15985

WARNINGS

1.Before use, perform a skin test on your arm and discontinue use if you have allergy symptoms or skin abnormalities.
2、For external use only, avoid contact with eyes when used
3、Keep out of reach of children

INDICATIONS AND USAGE

Wash vour face with water, applvan appropriate amount ofcream to the face, gently massage until absorbed.

DOSAGE AND ADMINISTRATION

applvan appropriate amount ofcream to the face, gently massage until absorbed.

KEEP OUT OF REACH OF CHILDREN SECTION

ACTIVE INGREDIENT

CARICA PAPAYA FRUIT EXTRACT2%
CARICA PAPAYA SEED OIL3%

PACKAGE LABEL

Active Ingredients
CARICA PAPAYA FRUIT EXTRACT2%
CARICA PAPAYA SEED OIL3%
SODIUM HYALURONATE1%

Uses：
For Facial Skin Moisturizing, Antioxidant, Blemish Removal, Whitening, Brightening
The storage method：
Store sealed in a cool place and out of sunlight

Warning.
1.Before use, perform a skin test on your arm and discontinue use if you have allergy symptoms or skin abnormalities.
2、For external use only, avoid contact with eyes when used
3、Keep out of reach of children